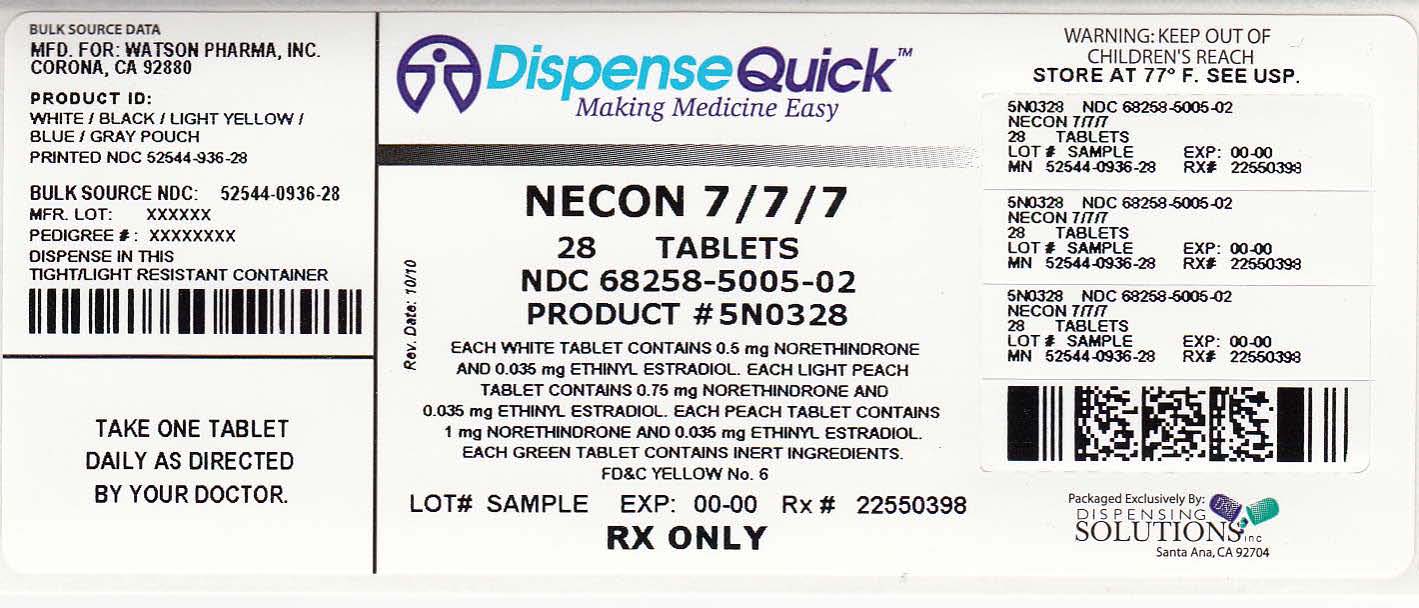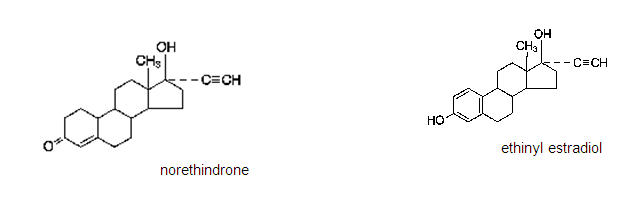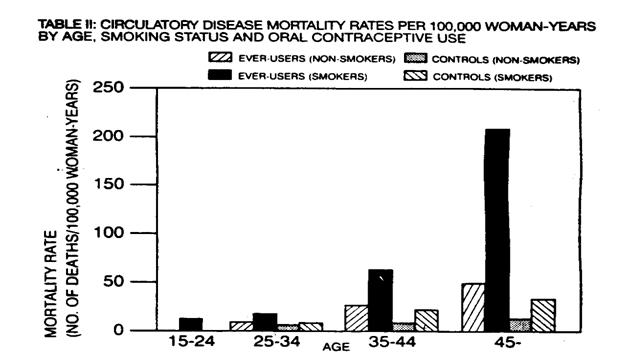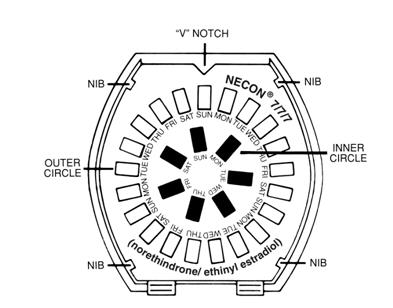 DRUG LABEL: Necon 777
NDC: 68258-5005 | Form: KIT | Route: ORAL
Manufacturer: Dispensing Solutions, Inc.
Category: prescription | Type: HUMAN PRESCRIPTION DRUG LABEL
Date: 20111006

ACTIVE INGREDIENTS: norethindrone 0.5 mg/1 1; ethinyl estradiol 0.035 mg/1 1; norethindrone 0.75 mg/1 1; ethinyl estradiol 0.035 mg/1 1; norethindrone 1 mg/1 1; ethinyl estradiol 0.035 mg/1 1
INACTIVE INGREDIENTS: LACTOSE; MAGNESIUM STEARATE; STARCH, CORN; FD&C YELLOW No. 6; LACTOSE; MAGNESIUM STEARATE; STARCH, CORN; FD&C YELLOW No. 6; LACTOSE; MAGNESIUM STEARATE; STARCH, CORN; D&C YELLOW No. 10; FD&C BLUE No. 2 ; ALUMINUM OXIDE; LACTOSE; MAGNESIUM STEARATE; CELLULOSE, MICROCRYSTALLINE; STARCH, CORN

NECON 7/7/7® Tablets
(norethindrone/ethinyl estradiol)

Patients should be counseled that this product does not protect against HIV infection (AIDS) and other sexually transmitted diseases.

COMBINED ORAL CONTRACEPTIVES

The following product is a combined oral contraceptive containing the progestational compound norethindrone and the estrogenic compound ethinyl estradiol.

NECON 7/7/7® Tablets: Each white tablet contains 0.5 mg of norethindrone and 0.035 mg of ethinyl estradiol. Inactive ingredients include lactose, magnesium stearate and pregelatinized corn starch. Each light peach tablet contains 0.75 mg of norethindrone and 0.035 mg of ethinyl estradiol. Inactive ingredients include FD&C Yellow No. 6, lactose, magnesium stearate and pregelatinized corn starch. Each peach tablet contains 1 mg of norethindrone and 0.035 mg of ethinyl estradiol. Inactive ingredients include FD&C Yellow No. 6, lactose, magnesium stearate and pregelatinized corn starch. Each green tablet contains only inert ingredients, as follows: D&C Yellow No. 10 Aluminum Lake, FD&C Blue No. 2 Aluminum Lake, lactose, magnesium stearate, microcrystalline cellulose and pregelatinized corn starch.

The chemical name for norethindrone is 17-Hydroxy-19-nor-17α-pregn-4-en-20-yn-3-one, and for ethinyl estradiol is 19-Nor-17α-pregna-1,3,5(10)-trien-20-yne-3,17-diol. Their structural formulas are as follows:

CLINICAL PHARMACOLOGY

Combined oral contraceptives act by suppression of gonadotropins. Although the primary mechanism of this action is inhibition of ovulation, other alterations include changes in the cervical mucus (which increase the difficulty of sperm entry into the uterus) and the endometrium (which reduce the likelihood of implantation).

INDICATIONS AND USAGE

NECON 7/7/7® Tablets are indicated for the prevention of pregnancy in women who elect to use this product as a method of contraception.

Oral contraceptives are highly effective. Table I lists the typical accidental pregnancy rates for users of combined oral contraceptives and other methods of contraception. The efficacy of these contraceptive methods, except sterilization, the IUD, and the NORPLANT® System depends upon the reliability with which they are used. Correct and consistent use of methods can result in lower failure rates.

TABLE I: PERCENTAGE OF WOMEN EXPERIENCING AN UNINTENDED PREGNANCY DURING THE FIRST YEAR OF TYPICAL USE AND THE FIRST YEAR OF PERFECT USE OF CONTRACEPTION AND THE PERCENTAGE CONTINUING USE AT THE END OF THE FIRST YEAR. UNITED STATES.
 | % of Women Experiencing an Unintended Pregnancy within the First Year of Use |  | % of Women Continuing Use at One Year
Method (1) | Typical Use (2) | Perfect Use (3) | (4)
Chance [The percents becoming pregnant in columns (2) and (3) are based on data from populations where contraception is not used and from women who cease using contraception in order to become pregnant. Among such populations, about 89% become pregnant within one year. This estimate was lowered slightly (to 85%) to represent the percent who would become pregnant within one year among women now relying on reversible methods of contraception if they abandoned contraception altogether.] | 85 | 85
Spermicides [Foams, creams, gels, vaginal suppositories, and vaginal film.] | 26 | 6 | 40
Periodic abstinence | 25 |  | 63
Calendar |  | 9
Ovulation Method |  | 3
Sympto-Thermal [Cervical mucus (ovulation) method supplemented by calendar in the pre-ovulatory and basal body temperature in the post-ovulatory phases.] |  | 2
Post-Ovulation |  | 1
Cap [With spermicidal cream or jelly.]
Parous Women | 40 | 26 | 42
Nulliparous Women | 20 | 9 | 56
Sponge
Parous Women | 40 | 20 | 42
Nulliparous Women | 20 | 9 | 56
Diaphragm | 20 | 6 | 56
Withdrawal | 19 | 4
Condom [Without spermicides.]
Female (Reality®) | 21 | 5 | 56
Male | 14 | 3 | 61
Pill | 5 |  | 71
Progestin Only |  | 0.5
Combined |  | 0.1
IUD
Progesterone T | 2.0 | 1.5 | 81
Copper T380A | 0.8 | 0.6 | 78
LNg 20 | 0.1 | 0.1 | 81
Depo-Provera® | 0.3 | 0.3 | 70
Norplant® and Norplant-2® | 0.05 | 0.05 | 88
Female Sterilization | 0.5 | 0.5 | 100
Male Sterilization | 0.15 | 0.10 | 100
Adapted from Hatcher et al., 1998, Ref. # 1.
Emergency Contraceptive Pills: Treatment initiated within 72 hours after unprotected intercourse reduces the risk or pregnancy by at least 75%. [The treatment schedule is one dose within 72 hours after unprotected intercourse, and a second dose 12 hours after the first dose. The FDA has declared the following brands of oral contraceptives to be safe and effective for emergency contraception: Ovral® (1 dose is 2 white pills), Alesse® (1 dose is 5 pink pills), Nordette® or Levlen® (1 dose is 2 light-orange pills), Lo/Ovral® (1 dose is 4 white pills), Triphasil® or Tri-Levlen® (1 dose is 4 yellow pills).]
Lactation Amenorrhea Method: LAM is a highly effective, temporary method of contraception. [However, to maintain effective protection against pregnancy, another method of contraception must be used as soon as menstruation resumes, the frequency or duration of breastfeeds is reduced, bottle feeds are introduced, or the baby reaches 6 months of age.]
Source: Trussell J. Contraceptive efficacy. In Hatchter RA, Trussell J, Stewart F, Cates W, Stewart GK, Kowal D, Guest F. Contraceptive Technology: Seventeenth Revised Edition. New York, NY: Irvington Publishers, 1998.

NECON 7/7/7® has not been studied for and is not indicated for use in emergency contraception.

CONTRAINDICATIONS

Oral contraceptives should not be used in women who currently have the following conditions:

- Thrombophlebitis or thromboembolic disorders
- A past history of deep vein thrombophlebitis or thromboembolic disorders
- Cerebral vascular or coronary artery disease (current or history)
- Valvular heart disease with complications
- Severe hypertension
- Diabetes with vascular involvement
- Headaches with focal neurological symptoms
- Major surgery with prolonged immobilization
- Known or suspected carcinoma of the breast
- Carcinoma of the endometrium or other known or suspected estrogen-dependent neoplasia
- Undiagnosed abnormal genital bleeding
- Cholestatic jaundice of pregnancy or jaundice with prior pill use
- Acute or chronic hepatocellular disease with abnormal liver function
- Hepatic adenomas or carcinomas
- Known or suspected pregnancy
- Hypersensitivity to any component of this product

WARNINGS

BOXED WARNING

Cigarette smoking increases the risk of serious cardiovascular side effects from oral contraceptive use. This risk increases with age and with heavy smoking (15 or more cigarettes per day) and is quite marked in women over 35 years of age. Women who use oral contraceptives should be strongly advised not to smoke.

The use of oral contraceptives is associated with increased risks of several serious conditions including myocardial infarction, thromboembolism, stroke, hepatic neoplasia, and gallbladder disease, although the risk of serious morbidity or mortality is very small in healthy women without underlying risk factors. The risk of morbidity and mortality increases significantly in the presence of other underlying risk factors such as hypertension, hyperlipidemias, obesity and diabetes.

Practitioners prescribing oral contraceptives should be familiar with the following information relating to these risks.

The information contained in this package insert is principally based on studies carried out in patients who used oral contraceptives with higher formulations of estrogens and progestogens than those in common use today. The effect of long-term use of the oral contraceptives with lower formulations of both estrogens and progestogens remains to be determined.

Throughout this labeling, epidemiological studies reported are of two types: retrospective or case control studies and prospective or cohort studies. Case control studies provide a measure of the relative risk of a disease, namely, a ratio of the incidence of a disease among oral contraceptive users to that among nonusers. The relative risk does not provide information on the actual clinical occurrence of a disease. Cohort studies provide a measure of attributable risk, which is the difference in the incidence of disease between oral contraceptive users and nonusers. The attributable risk does provide information about the actual occurrence of a disease in the population (adapted from refs. 2 and 3 with the author's permission). For further information, the reader is referred to a text on epidemiological methods.

1. THROMBOEMBOLIC DISORDERS AND OTHER VASCULAR PROBLEMS

a. Myocardial Infarction

An increased risk of myocardial infarction has been attributed to oral contraceptive use. This risk is primarily in smokers or women with other underlying risk factors for coronary artery disease such as hypertension, hypercholesterolemia, morbid obesity, and diabetes. The relative risk of heart attack for current oral contraceptive users has been estimated to be two to six.^4–10 The risk is very low under the age of 30.

Smoking in combination with oral contraceptive use has been shown to contribute substantially to the incidence of myocardial infarctions in women in their mid-thirties or older with smoking accounting for the majority of excess cases.^11 Mortality rates associated with circulatory disease have been shown to increase substantially in smokers, especially in those 35 years of age and older, and in nonsmokers over the age of 40 among women who use oral contraceptives.

(Adapted from P.M. Layde and V. Beral, ref. #12.)

Oral contraceptives may compound the effects of well-known risk factors, such as hypertension, diabetes, hyperlipidemias, age and obesity.^13 In particular, some progestogens are known to decrease HDL cholesterol and cause glucose intolerance, while estrogens may create a state of hyperinsulinism.^14–18 Oral contraceptives have been shown to increase blood pressure among users (see Section 9 in WARNINGS). Similar effects on risk factors have been associated with an increased risk of heart disease. Oral contraceptives must be used with caution in women with cardiovascular disease risk factors.

b. Thromboembolism

An increased risk of thromboembolic and thrombotic disease associated with the use of oral contraceptives is well established. Case control studies have found the relative risk of users compared to nonusers to be 3 for the first episode of superficial venous thrombosis, 4 to 11 for deep vein thrombosis or pulmonary embolism, and 1.5 to 6 for women with predisposing conditions for venous thromboembolic disease.^2,3,19–24 Cohort studies have shown the relative risk to be somewhat lower, about 3 for new cases and about 4.5 for new cases requiring hospitalization.^25 The risk of thromboembolic disease associated with oral contraceptives is not related to length of use and disappears after pill use is stopped.^2

A two- to four-fold increase in relative risk of post-operative thromboembolic complications has been reported with the use of oral contraceptives.^9 The relative risk of venous thrombosis in women who have predisposing conditions is twice that of women without such medical conditions.^26 If feasible, oral contraceptives should be discontinued at least four weeks prior to and for two weeks after elective surgery of a type associated with an increase in risk of thromboembolism and during and following prolonged immobilization. Since the immediate postpartum period is also associated with an increased risk of thromboembolism, oral contraceptives should be started no earlier than four weeks after delivery in women who elect not to breastfeed.

c. Cerebrovascular diseases

Oral contraceptives have been shown to increase both the relative and attributable risks of cerebrovascular events (thrombotic and hemorrhagic strokes), although, in general, the risk is greatest among older (>35 years), hypertensive women who also smoke. Hypertension was found to be a risk factor for both users and nonusers, for both types of strokes, and smoking interacted to increase the risk of stroke.^27–29

In a large study, the relative risk of thrombotic strokes has been shown to range from 3 for normotensive users to 14 for users with severe hypertension.^30 The relative risk of hemorrhagic stroke is reported to be 1.2 for non-smokers who used oral contraceptives, 2.6 for smokers who did not use oral contraceptives, 7.6 for smokers who used oral contraceptives, 1.8 for normotensive users and 25.7 for users with severe hypertension.^30 The attributable risk is also greater in older women.^3

d. Dose-related risk of vascular disease from oral contraceptives

A positive association has been observed between the amount of estrogen and progestogen in oral contraceptives and the risk of vascular disease.^31–33 A decline in serum high density lipoproteins (HDL) has been reported with many progestational agents.^14–16 A decline in serum high density lipoproteins has been associated with an increased incidence of ischemic heart disease. Because estrogens increase HDL cholesterol, the net effect of an oral contraceptive depends on a balance achieved between doses of estrogen and progestogen and the activity of the progestogen used in the contraceptives. The activity and amount of both hormones should be considered in the choice of an oral contraceptive.

Minimizing exposure to estrogen and progestogen is in keeping with good principles of therapeutics. For any particular estrogen/progestogen combination, the dosage regimen prescribed should be one which contains the least amount of estrogen and progestogen that is compatible with a low failure rate and the needs of the individual patient. New acceptors of oral contraceptive agents should be started on preparations containing the lowest estrogen content which is judged appropriate for the individual patient.

e. Persistence of risk of vascular disease

There are two studies which have shown persistence of risk of vascular disease for ever-users of oral contraceptives. In a study in the United States, the risk of developing myocardial infarction after discontinuing oral contraceptives persists for at least 9 years for women 40–49 years who had used oral contraceptives for five or more years, but this increased risk was not demonstrated in other age groups.^8 In another study in Great Britain, the risk of developing cerebrovascular disease persisted for at least 6 years after discontinuation of oral contraceptives, although excess risk was very small.^34 However, both studies were performed with oral contraceptive formulations containing 50 micrograms or higher of estrogens.

2. ESTIMATES OF MORTALITY FROM CONTRACEPTIVE USE

One study gathered data from a variety of sources which have estimated the mortality rate associated with different methods of contraception at different ages (Table III). These estimates include the combined risk of death associated with contraceptive methods plus the risk attributable to pregnancy in the event of method failure. Each method of contraception has its specific benefits and risks. The study concluded that with the exception of oral contraceptive users 35 and older who smoke, and 40 and older who do not smoke, mortality associated with all methods of birth control is low and below that associated with childbirth. The observation of an increase in risk of mortality with age for oral contraceptive users is based on data gathered in the 1970's.^35 Current clinical recommendation involves the use of lower estrogen dose formulations and a careful consideration of risk factors. In 1989, the Fertility and Maternal Health Drugs Advisory Committee was asked to review the use of oral contraceptives in women 40 years of age and over. The Committee concluded that although cardiovascular disease risks may be increased with oral contraceptive use after age 40 in healthy non-smoking women (even with the newer low-dose formulations), there are also greater potential health risks associated with pregnancy in older women and with the alternative surgical and medical procedures which may be necessary if such women do not have access to effective and acceptable means of contraception. The Committee recommended that the benefits of low-dose oral contraceptive use by healthy non-smoking women over 40 may outweigh the possible risks.

Of course, older women, as all women who take oral contraceptives, should take an oral contraceptive which contains the least amount of estrogen and progestogen that is compatible with a low failure rate and individual patient needs.

TABLE III: ANNUAL NUMBER OF BIRTH-RELATED OR METHOD-RELATED DEATHS ASSOCIATED WITH CONTROL OF FERTILITY PER 100,000 NONSTERILE WOMEN, BY FERTILITY CONTROL METHOD ACCORDING TO AGE
Method of control and outcome | 15–19 | 20–24 | 25–29 | 30–34 | 35–39 | 40–44
No fertility-control methods [Deaths are birth-related] | 7.0 | 7.4 | 9.1 | 14.8 | 25.7 | 28.2
Oral contraceptives non-smoker [Deaths are method-related] | 0.3 | 0.5 | 0.9 | 1.9 | 13.8 | 31.6
Oral contraceptives smoker | 2.2 | 3.4 | 6.6 | 13.5 | 51.1 | 117.2
IUD | 0.8 | 0.8 | 1.0 | 1.0 | 1.4 | 1.4
Condom | 1.1 | 1.6 | 0.7 | 0.2 | 0.3 | 0.4
Diaphragm/spermicide | 1.9 | 1.2 | 1.2 | 1.3 | 2.2 | 2.8
Periodic abstinence | 2.5 | 1.6 | 1.6 | 1.7 | 2.9 | 3.6
Adapted from H.W. Ory, ref. #35.

3. CARCINOMA OF THE REPRODUCTIVE ORGANS AND BREASTS

Numerous epidemiological studies have been performed on the incidence of breast, endometrial, ovarian and cervical cancer in women using oral contraceptives. The risk of having breast cancer diagnosed may be slightly increased among current and recent users of COCs. However, this excess risk appears to decrease over time after COC discontinuation and by 10 years after cessation the increased risk disappears. Some studies report an increased risk with duration of use while other studies do not and no consistent relationships have been found with dose or type of steroid. Some studies have found a small increase in risk for women who first use COCs before age 20. Most studies show a similar pattern of risk with COC use regardless of a woman's reproductive history or her family breast cancer history.

Breast cancers diagnosed in current or previous OC users tend to be less clinically advanced than in nonusers.

Women who currently have or have had breast cancer should not use oral contraceptives because breast cancer is usually a hormonally-sensitive tumor.

Some studies suggest that oral contraceptive use has been associated with an increase in the risk of cervical intraepithelial neoplasia in some populations of women.^45–48 However, there continues to be controversy about the extent to which such findings may be due to differences in sexual behavior and other factors.

In spite of many studies of the relationship between oral contraceptive use and breast and cervical cancers, a cause-and-effect relationship has not been established.

4. HEPATIC NEOPLASIA

Benign hepatic adenomas are associated with oral contraceptive use, although the incidence of benign tumors is rare in the United States. Indirect calculations have estimated the attributable risk to be in the range of 3.3 cases/100,000 for users, a risk that increases after four or more years of use especially with oral contraceptives of higher dose.^49 Rupture of benign, hepatic adenomas may cause death through intra-abdominal hemorrhage.^(50, 51)

Studies from Britain have shown an increased risk of developing hepatocellular carcinoma in long-term (>8 years) oral contraceptive users. However, these cancers are extremely rare in the U.S. and the attributable risk (the excess incidence) of liver cancers in oral contraceptive users approaches less than one per million users.

5. OCULAR LESIONS

There have been clinical case reports of retinal thrombosis associated with the use of oral contraceptives. Oral contraceptives should be discontinued if there is unexplained partial or complete loss of vision; onset of proptosis or diplopia; papilledema; or retinal vascular lesions. Appropriate diagnostic and therapeutic measures should be undertaken immediately.

6. ORAL CONTRACEPTIVE USE BEFORE OR DURING EARLY PREGNANCY

Extensive epidemiological studies have revealed no increased risk of birth defects in women who have used oral contraceptives prior to pregnancy.^56,57 The majority of recent studies also do not indicate a teratogenic effect, particularly in so far as cardiac anomalies and limb reduction defects are concerned,^55,56,58,59 when taken inadvertently during early pregnancy.

The administration of oral contraceptives to induce withdrawal bleeding should not be used as a test for pregnancy. Oral contraceptives should not be used during pregnancy to treat threatened or habitual abortion.

It is recommended that for any patient who has missed two consecutive periods, pregnancy should be ruled out. If the patient has not adhered to the prescribed schedule, the possibility of pregnancy should be considered at the time of the first missed period. Oral contraceptive use should be discontinued if pregnancy is confirmed.

7. GALLBLADDER DISEASE

Earlier studies have reported an increased lifetime relative risk of gallbladder surgery in users of oral contraceptives and estrogens.^(60, 61) More recent studies, however, have shown that the relative risk of developing gallbladder disease among oral contraceptive users may be minimal.^62–64 The recent findings of minimal risk may be related to the use of oral contraceptive formulations containing lower hormonal doses of estrogens and progestogens.

8. CARBOHYDRATE AND LIPID METABOLIC EFFECTS

Oral contraceptives have been shown to cause a decrease in glucose tolerance in a significant percentage of users.^17 This effect has been shown to be directly related to estrogen dose.^65 Progestogens increase insulin secretion and create insulin resistance, this effect varying with different progestational agents.^17,66 However, in the non-diabetic woman, oral contraceptives appear to have no effect on fasting blood glucose.^67 Because of these demonstrated effects, prediabetic and diabetic women in particular should be carefully monitored while taking oral contraceptives.

A small proportion of women will have persistent hypertriglyceridemia while on the pill. As discussed earlier (see WARNINGS 1a and 1d), changes in serum triglycerides and lipoprotein levels have been reported in oral contraceptive users.

9. ELEVATED BLOOD PRESSURE

Women with significant hypertension should not be started on hormonal contraception.^92 An increase in blood pressure has been reported in women taking oral contraceptives^68 and this increase is more likely in older oral contraceptive users^69 and with extended duration of use.^61 Data from the Royal College of General Practitioners^12 and subsequent randomized trials have shown that the incidence of hypertension increases with increasing progestational activity.

Women with a history of hypertension or hypertension-related diseases, or renal disease^70 should be encouraged to use another method of contraception. If women elect to use oral contraceptives, they should be monitored closely and if significant elevation of blood pressure occurs, oral contraceptives should be discontinued. For most women, elevated blood pressure will return to normal after stopping oral contraceptives, and there is no difference in the occurrence of hypertension between former and never users.^68–71

10. HEADACHE

The onset or exacerbation of migraine or development of headache with a new pattern which is recurrent, persistent or severe requires discontinuation of oral contraceptives and evaluation of the cause.

11. BLEEDING IRREGULARITIES

Breakthrough bleeding and spotting are sometimes encountered in patients on oral contraceptives, especially during the first three months of use. Nonhormonal causes should be considered and adequate diagnostic measures taken to rule out malignancy or pregnancy in the event of breakthrough bleeding, as in the case of any abnormal vaginal bleeding. If pathology has been excluded, time or a change to another formulation may solve the problem. In the event of amenorrhea, pregnancy should be ruled out.

Some women may encounter post-pill amenorrhea or oligomenorrhea, especially when such a condition was preexistent.

12. ECTOPIC PREGNANCY

Ectopic as well as intrauterine pregnancy may occur in contraceptive failures.

PRECAUTIONS

1. GENERAL

Patients should be counseled that this product does not protect against HIV infection (AIDS) and other sexually transmitted diseases.

2. PHYSICAL EXAMINATION AND FOLLOW-UP

It is good medical practice for all women to have annual history and physical examinations, including women using oral contraceptives. The physical examination, however, may be deferred until after initiation of oral contraceptives if requested by the woman and judged appropriate by the clinician. The physical examination should include special reference to blood pressure, breasts, abdomen and pelvic organs, including cervical cytology, and relevant laboratory tests. In case of undiagnosed, persistent or recurrent abnormal vaginal bleeding, appropriate measures should be conducted to rule out malignancy. Women with a strong family history of breast cancer or who have breast nodules should be monitored with particular care.

3. LIPID DISORDERS

Women who are being treated for hyperlipidemias should be followed closely if they elect to use oral contraceptives. Some progestogens may elevate LDL levels and may render the control of hyperlipidemias more difficult.

4. LIVER FUNCTION

If jaundice develops in any woman receiving such drugs, the medication should be discontinued. Steroid hormones may be poorly metabolized in patients with impaired liver function.

5. FLUID RETENTION

Oral contraceptives may cause some degree of fluid retention. They should be prescribed with caution, and only with careful monitoring, in patients with conditions which might be aggravated by fluid retention.

6. EMOTIONAL DISORDERS

Women with a history of depression should be carefully observed and the drug discontinued if depression recurs to a serious degree.

7. CONTACT LENSES

Contact lens wearers who develop visual changes or changes in lens tolerance should be assessed by an ophthalmologist.

8. DRUG INTERACTIONS

Changes in contraceptive effectiveness associated with co-administration of other products

Contraceptive effectiveness may be reduced when hormonal contraceptives are co-administered with antibiotics, anticonvulsants, and other drugs that increase the metabolism of contraceptive steroids. This could result in unintended pregnancy or breakthrough bleeding. Examples include rifampin, barbiturates, phenylbutazone, phenytoin, carbamazepine, felbamate, oxcarbazepine, topiramate, griseofulvin and bosentan. Several cases of contraceptive failure and breakthrough bleeding have been reported in the literature with concomitant administration of antibiotics such as ampicillin and tetracyclines. However, clinical pharmacology studies investigating drug interaction between combined oral contraceptives and these antibiotics have reported inconsistent results.

Several of the anti-HIV protease inhibitors have been studied with co-administration of oral combined hormonal contraceptives; significant changes (increase and decrease) in the plasma levels of the estrogen and progestin have been noted in some cases. The safety and efficacy of oral contraceptive products may be affected with co-administration of anti-HIV protease inhibitors. Healthcare professionals should refer to the label of the individual anti-HIV protease inhibitors for further drug-drug interaction information.

Herbal products containing St. John's Wort (hypericum perforatum) may induce hepatic enzymes (cytochrome P450) and p-glycoprotein transporter and may reduce the effectiveness of contraceptive steroids. This may also result in breakthrough bleeding.

Concurrent use of bosentan and norethisterone/ethinyl estradiol may result in decreased concentrations of these contraceptive hormones, thereby increasing the risk of unintended pregnancy and unscheduled bleeding.

Increase in plasma levels associated with co-administered drugs

Co-administration of atorvastatin and certain oral contraceptives containing ethinyl estradiol increase AUC values for ethinyl estradiol by approximately 20%. Ascorbic acid and acetaminophen may increase plasma ethinyl estradiol levels, possibly by inhibition of conjugation. CYP 3A4 inhibitors such as itraconazole or ketoconazole may increase plasma hormone levels.

Changes in plasma levels of co-administered drugs

Combined hormonal contraceptives containing some synthetic estrogens (e.g., ethinyl estradiol) may inhibit the metabolism of other compounds. Increased plasma concentrations of cyclosporin, prednisolone, and theophylline have been reported with concomitant administration of oral contraceptives. Decreased plasma concentrations of acetaminophen and increased clearance of temazepam, salicylic acid, morphine and clofibric acid, due to induction of conjugation, have been noted when these drugs were administered with oral contraceptives.

Combined hormonal contraceptives have been shown to significantly decrease plasma concentrations of lamotrigine when co-administered due to induction of lamotrigine glucuronidation. This may reduce seizure control; therefore, dosage adjustments of lamotrigine may be necessary.^95

Healthcare professionals are advised to also refer to prescribing information of co-administered drugs for recommendations regarding management of concomitant therapy.

9. INTERACTIONS WITH LABORATORY TESTS

Certain endocrine and liver function tests and blood components may be affected by oral contraceptives:

1. Increased prothrombin and factors VII, VIII, IX, and X; decreased antithrombin 3; increased norepinephrine-induced platelet aggregability.
2. Increased thyroid binding globulin (TBG) leading to increased circulating total thyroid hormone, as measured by protein-bound iodine (PBI), T4 by column or by radioimmunoassay. Free T3 resin uptake is decreased, reflecting the elevated TBG, free T4 concentration is unaltered.
3. Other binding proteins may be elevated in serum.
4. Sex-binding globulins are increased and result in elevated levels of total circulating sex steroids and corticoids; however, free or biologically active levels remain unchanged.
5. Triglycerides may be increased and levels of various other lipids and lipoproteins may be affected.
6. Glucose tolerance may be decreased.
7. Serum folate levels may be depressed by oral contraceptive therapy. This may be of clinical significance if a woman becomes pregnant shortly after discontinuing oral contraceptives.

10. CARCINOGENESIS

See WARNINGS.

11. PREGNANCY

Pregnancy Category X

See CONTRAINDICATIONS and WARNINGS.

12. NURSING MOTHERS

Small amounts of oral contraceptive steroids have been identified in the milk of nursing mothers and a few adverse effects on the child have been reported, including jaundice and breast enlargement. In addition, combined oral contraceptives given in the postpartum period may interfere with lactation by decreasing the quantity and quality of breast milk. If possible, the nursing mother should be advised not to use combined oral contraceptives but to use other forms of contraception until she has completely weaned her child.

13. PEDIATRIC USE

Safety and efficacy of NECON 7/7/7® Tablets have been established in women of reproductive age. Safety and efficacy are expected to be the same for postpubertal adolescents under the age of 16 and for users 16 years and older. Use of this product before menarche is not indicated.

14. GERIATRIC USE

This product has not been studied in women over 65 years of age and is not indicated in this population.

INFORMATION FOR THE PATIENT

See Patient Labeling printed below.

ADVERSE REACTIONS

An increased risk of the following serious adverse reactions has been associated with the use of oral contraceptives (See WARNINGS).

- Thrombophlebitis and venous thrombosis with or without embolism
- Arterial thromboembolism
- Pulmonary embolism
- Myocardial infarction
- Cerebral hemorrhage
- Cerebral thrombosis
- Hypertension
- Gallbladder disease
- Hepatic adenomas or benign liver tumors

There is evidence of an association between the following conditions and the use of oral contraceptives:

- Mesenteric thrombosis
- Retinal thrombosis

The following adverse reactions have been reported in patients receiving oral contraceptives and are believed to be drug-related:

- Nausea
- Vomiting
- Gastrointestinal symptoms (such as abdominal cramps and bloating)
- Breakthrough bleeding
- Spotting
- Change in menstrual flow
- Amenorrhea
- Temporary infertility after discontinuation of treatment
- Edema
- Melasma which may persist
- Breast changes: tenderness, enlargement, secretion
- Change in weight (increase or decrease)
- Change in cervical erosion and secretion
- Diminution in lactation when given immediately postpartum
- Cholestatic jaundice
- Migraine
- Allergic reaction, including rash, urticaria, angioedema
- Mental depression
- Reduced tolerance to carbohydrates
- Vaginal candidiasis
- Change in corneal curvature (steepening)
- Intolerance to contact lenses

The following adverse reactions have been reported in users of oral contraceptives and a causal association has been neither confirmed nor refuted:

- Pre-menstrual syndrome
- Cataracts
- Changes in appetite
- Cystitis-like syndrome
- Headache
- Nervousness
- Dizziness
- Hirsutism
- Loss of scalp hair
- Erythema multiforme
- Erythema nodosum
- Hemorrhagic eruption
- Vaginitis
- Porphyria
- Impaired renal function
- Hemolytic uremic syndrome
- Acne
- Changes in libido
- Colitis
- Budd-Chiari Syndrome

OVERDOSAGE

Serious ill effects have not been reported following acute ingestion of large doses of oral contraceptives by young children. Overdosage may cause nausea, and withdrawal bleeding may occur in females.

NON-CONTRACEPTIVE HEALTH BENEFITS

The following non-contraceptive health benefits related to the use of combined oral contraceptives are supported by epidemiological studies which largely utilized oral contraceptive formulations containing estrogen doses exceeding 0.035 mg of ethinyl estradiol or 0.05 mg mestranol.^73–78

Effects on menses:

- increased menstrual cycle regularity
- decreased blood loss and decreased incidence of iron deficiency anemia
- decreased incidence of dysmenorrhea

Effects related to inhibition of ovulation:

- decreased incidence of functional ovarian cysts
- decreased incidence of ectopic pregnancies

Other effects:

- decreased incidence of fibroadenomas and fibrocystic disease of the breast
- decreased incidence of acute pelvic inflammatory disease
- decreased incidence of endometrial cancer
- decreased incidence of ovarian cancer

DOSAGE AND ADMINISTRATION

To achieve maximum contraceptive effectiveness, NECON 7/7/7® Tablets must be taken exactly as directed and at intervals not exceeding 24 hours. NECON 7/7/7® Tablets are available in a blister card with a tablet dispenser which is preset for a Sunday Start. Day 1 Start is also available.

Sunday Start

When taking NECON 7/7/7®, the first white "active" tablet should be taken on the first Sunday after menstruation begins. If the period begins on Sunday, the first white "active" tablet should be taken that day. Take one active tablet daily for 21 days followed by one green "reminder" tablet daily for 7 days. After 28 tablets have been taken, a new course is started the next day (Sunday). For the first cycle of a Sunday Start regimen, another method of contraception, such as a condom or spermicide, should be used until after the first 7 consecutive days of administration.

If the patient misses one (1) active tablet in Weeks 1, 2, or 3, the tablet should be taken as soon as she remembers. If the patient misses two (2) active tablets in Week 1 or Week 2, the patient should take two (2) tablets the day she remembers and two (2) tablets the next day; and then continue taking one (1) tablet a day until she finishes the pack. The patient should be instructed to use a back-up method of birth control, such as a condom or spermicide, if she has sex in the seven (7) days after missing pills. If the patient misses two (2) active tablets in the third week or misses three (3) or more active tablets in a row, the patient should continue taking one tablet every day until Sunday. On Sunday the patient should throw out the rest of the pack and start a new pack that same day. The patient should be instructed to use a back-up method of birth control if she has sex in the seven (7) days after missing pills.

Complete instructions to facilitate patient counseling on proper pill usage may be found in the Detailed Patient Labeling ("How to Take the Pill" section).

Day 1 Start

The dosage of NECON 7/7/7® for the initial cycle of therapy is one active tablet administered daily from the 1st through the 21st day of the menstrual cycle, counting the first day of menstrual flow as "Day 1" followed by one green "reminder" tablet daily for 7 days. Tablets are taken without interruption for 28 days. After 28 tablets have been taken, a new course is started the next day.

If the patient misses one (1) active tablet in Weeks 1, 2, or 3, the tablet should be taken as soon as she remembers. If the patient misses two (2) active tablets in Week 1 or Week 2, the patient should take two (2) tablets the day she remembers and two (2) tablets the next day; and then continue taking one (1) tablet a day until she finishes the pack. The patient should be instructed to use a back-up method of birth control, such as a condom or spermicide, if she has sex in the seven (7) days after missing pills. If the patient misses two (2) active tablets in the third week or misses three (3) or more active tablets in a row, the patient should throw out the rest of the pack and start a new pack that same day. The patient should be instructed to use a back-up method of birth control if she has sex in the seven (7) days after missing pills.

Complete instructions to facilitate patient counseling on proper pill usage may be found in the Detailed Patient Labeling ("How to Take the Pill" section).

The use of NECON 7/7/7® for contraception may be initiated 4 weeks postpartum in women who elect not to breastfeed. When the tablets are administered during the postpartum period, the increased risk of thromboembolic disease associated with the postpartum period must be considered. (See CONTRAINDICATIONS and WARNINGS concerning thromboembolic disease. See also PRECAUTIONS: Nursing Mothers.) The possibility of ovulation and conception prior to initiation of medication should be considered.

(See Discussion of Dose-Related Risk of Vascular Disease from Oral Contraceptives.)

ADDITIONAL INSTRUCTIONS

Breakthrough bleeding, spotting, and amenorrhea are frequent reasons for patients discontinuing oral contraceptives. In breakthrough bleeding, as in all cases of irregular bleeding from the vagina, nonfunctional causes should be borne in mind. In undiagnosed persistent or recurrent abnormal bleeding from the vagina, adequate diagnostic measures are indicated to rule out pregnancy or malignancy. If pathology has been excluded, time or a change to another formulation may solve the problem. Changing to an oral contraceptive with a higher estrogen content, while potentially useful in minimizing menstrual irregularity, should be done only if necessary since this may increase the risk of thromboembolic disease.

Use of oral contraceptives in the event of a missed menstrual period:

1. If the patient has not adhered to the prescribed schedule, the possibility of pregnancy should be considered at the time of the first missed period and oral contraceptive use should be discontinued if pregnancy is confirmed.
2. If the patient has adhered to the prescribed regimen and misses two consecutive periods, pregnancy should be ruled out.

HOW SUPPLIED

NECON 7/7/7® Tablets are available in a blister card (NDC 52544-936-28) with a tablet dispenser (unfilled). The blister card contains 28 tablets, as follows: 7 white, round, flat-faced, beveled edged tablets imprinted WATSON on one side and 937 on the other side (0.5 mg norethindrone and 0.035 mg ethinyl estradiol), 7 light peach, round, flat-faced, beveled edged tablets imprinted WATSON on one side and 938 on the other side (0.75 mg norethindrone and 0.035 mg ethinyl estradiol), 7 peach, round, flat-faced, beveled edged tablets imprinted WATSON on one side and 939 on the other side (1 mg norethindrone and 0.035 mg ethinyl estradiol) and 7 green, round, flat-faced, beveled edged tablets imprinted WATSON on one side and "P" on the other side containing inert ingredients.

STORAGE

Store at 25°C (77°F); excursions permitted to 15°–30°C (59°–86°F).

Keep out of reach of children.

REFERENCES

1. Trussell J. Contraceptive efficacy. In Hatcher RA, Trussell J, Stewart F, Cates W, Stewart GK, Kowal D, Guest F, Contraceptive Technology: Seventeenth Revised Edition. New York, NY: Irvington Publishers, 1998, in press.
2. Stadel BV, Oral contraceptives and cardiovascular disease. (Pt. 1). N Engl J Med 1981; 305:612–618.
3. Stadel BV, Oral contraceptives and cardiovascular disease. (Pt. 2). N Engl J Med 1981; 305:672–677.
4. Adam SA, Thorogood M. Oral contraception and myocardial infarction revisited: the effects of new preparations and prescribing patterns. Br J Obstet Gynaecol 1981; 88:838–845.
5. Mann JI, Inman WH. Oral contraceptives and death from myocardial infarction. Br Med J 1975; 2(5965):245–248.
6. Mann JI, Vessey MP, Thorogood M, Doll R. Myocardial infarction in young women with special reference to oral contraceptive practice. Br Med J 1975; 2(5956):241–245.
7. Royal College of General Practitioners' Oral Contraception Study: further analyses of mortality in oral contraceptive users. Lancet 1981; 1:541–546.
8. Slone D, Shapiro S, Kaufman DW, Rosenberg L, Miettinen OS, Stolley PD. Risk of myocardial infarction in relation to current and discontinued use of oral contraceptives. N Engl J Med 1981; 305:420–424.
9. Vessey MP. Female hormones and vascular disease-an epidemiological overview. Br J Fam Plann 1980; 6 (Supplement): 1–12.
10. Russell-Briefel RG, Ezzati TM, Fulwood R, Perlman JA, Murphy RS. Cardiovascular risk status and oral contraceptive use, United States, 1976–80. Prevent Med 1986; 15:352–362.
11. Goldbaum GM, Kendrick JS, Hogelin GC, Gentry EM. The relative impact of smoking and oral contraceptive use on women in the United States. JAMA 1987; 258:1339–1342.
12. Layde PM, Beral V. Further analyses of mortality in oral contraceptive users; Royal College of General Practitioners' Oral Contraception Study. (Table 5) Lancet 1981; 1:541–546.
13. Knopp RH. Arteriosclerosis risk: the roles of oral contraceptives and postmenopausal estrogens. J Reprod Med 1986; 31(9) (Supplement): 913–921.
14. Krauss RM, Roy S, Mishell DR, Casagrande J, Pike MC. Effects of two low-dose oral contraceptives on serum lipids and lipoproteins: Differential changes in high-density lipoproteins subclasses. Am J Obstet 1983; 145:446–452.
15. Wahl P, Walden C, Knopp R, Hoover J, Wallace R, Heiss G, Rifkind B. Effect of estrogen/progestin potency on lipid/lipoprotein cholesterol. N Engl J Med 1983; 308:862–867.
16. Wynn V, Niththyananthan R. The effect of progestin in combined oral contraceptives on serum lipids with special reference to high density lipoproteins. Am J Obstet Gynecol 1982; 142:766–771.
17. Wynn V, Godsland I. Effects of oral contraceptives on carbohydrate metabolism. J Reprod Med 1986; 31(9)(Supplement):892–897.
18. LaRosa JC. Atherosclerotic risk factors in cardiovascular disease. J Reprod Med 1986; 31(9)(Supplement):906–912.
19. Inman WH, Vessey MP. Investigation of death from pulmonary, coronary, and cerebral thrombosis and embolism in women of child-bearing age. Br Med J 1968; 2(5599):193–199.
20. Maguire MG, Tonascia J, Sartwell PE, Stolley PD, Tockman MS. Increased risk of thrombosis due to oral contraceptives: a further report. Am J Epidemiol 1979; 110(2):188–195.
21. Petitti DB, Wingerd J, Pellegrin F, Ramacharan S. Risk of vascular disease in women: smoking, oral contraceptives, noncontraceptive estrogens, and other factors. JAMA 1979; 242:1150–1154.
22. Vessey MP, Doll R. Investigation of relation between use of oral contraceptives and thromboembolic disease. Br Med J 1968; 2(5599):199–205.
23. Vessey MP, Doll R. Investigation of relation between use of oral contraceptives and thromboembolic disease. A further report. Br Med J 1969; 2(5658):651–657.
24. Porter JB, Hunter JR, Danielson DA, Jick H, Stergachis A. Oral contraceptives and non-fatal vascular disease-recent experience. Obstet Gynecol 1982; 59(3):299–302.
25. Vessey M, Doll R, Peto R, Johnson B, Wiggins P. A long-term follow-up study of women using different methods of contraception: an interim report. J Biosocial Sci 1976; 8:375–427.
26. Royal College of General Practitioners: Oral Contraceptives, venous thrombosis, and varicose veins. J Royal Coll Gen Pract 1978; 28:393–399.
27. Collaborative Group for the Study of Stroke in Young Women: Oral contraception and increased risk of cerebral ischemia or thrombosis. N Engl J Med 1973; 288:871–878.
28. Petitti DB, Wingerd J. Use of oral contraceptives, cigarette smoking, and risk of subarachnoid hemorrhage. Lancet 1978; 2:234–236.
29. Inman WH. Oral contraceptives and fatal subarachnoid hemorrhage. Br Med J 1979; 2(6203):1468–1470.
30. Collaborative Group for the Study of Stroke in Young Women: Oral Contraceptives and stroke in young women: associated risk factors. JAMA 1975; 231:718–722.
31. Inman WH, Vessey MP, Westerholm B, Engelund A. Thromboembolic disease and the steroidal content of oral contraceptives. A report to the Committee on Safety of Drugs. Br Med J 1970; 2:203–209.
32. Meade TW, Greenberg G, Thompson SG. Progestogens and cardiovascular reactions associated with oral contraceptives and a comparison of the safety of 50- and 35-mcg oestrogen preparations. Br Med J 1980; 280(6224):1157–1161.
33. Kay CR. Progestogens and arterial disease-evidence from the Royal College of General Practitioners' Study. Am J Obstet Gynecol 1982; 142:762–765.
34. Royal College of General Practitioners: Incidence of arterial disease among oral contraceptive users. J Royal Coll Gen Pract 1983; 33:75–82.
35. Ory HW. Mortality associated with fertility and fertility control: 1983. Family Planning Perspectives 1983; 15:50–56.
36. The Cancer and Steroid Hormone Study of the Centers for Disease Control and the National Institute of Child Health and Human Development: Oral contraceptive use and the risk of breast cancer. N Engl J Med 1986; 315:405–411.
37. Pike MC, Henderson BE, Krailo MD, Duke A, Roy S. Breast cancer in young women and use of oral contraceptives: possible modifying effect of formulation and age at use. Lancet 1983; 2:926–929.
38. Paul C, Skegg DG, Spears GFS, Kaldor JM. Oral contraceptives and breast cancer: A national study. Br Med J 1986; 293:723–725.
39. Miller DR, Rosenberg L, Kaufman DW, Schottenfeld D, Stolley PD, Shapiro S. Breast cancer risk in relation to early oral contraceptive use. Obstet Gynecol 1986; 68:863–868.
40. Olsson H, Olsson ML, Moller TR, Ranstam J, Holm P. Oral contraceptive use and breast cancer in young women in Sweden (letter). Lancet 1985; 1(8431):748–749.
41. McPherson K, Vessey M, Neil A, Doll R, Jones L, Roberts M. Early contraceptive use and breast cancer: Results of another case-control study. Br J Cancer 1987; 56:653–660.
42. Huggins GR, Zucker PF. Oral contraceptives and neoplasia: 1987 update. Fertil Steril 1987; 47:733–761.
43. McPherson K, Drife JO. The pill and breast cancer: why the uncertainty? Br Med J 1986; 293:709–710.
44. Shapiro S. Oral contraceptives-time to take stock. N Engl J Med 1987; 315:450–451.
45. Ory H, Naib Z, Conger SB, Hatcher RA, Tyler CW. Contraceptive choice and prevalence of cervical dysplasia and carcinoma in situ. Am J Obstet Gynecol 1976; 124:573–577.
46. Vessey MP, Lawless M, McPherson K, Yeates D. Neoplasia of the cervix uteri and contraception: a possible adverse effect of the pill. Lancet 1983; 2:930.
47. Brinton LA, Huggins GR, Lehman HF, Malli K, Savitz DA, Trapido E, Rosenthal J, Hoover R. Long term use of oral contraceptives and risk of invasive cervical cancer. Int J Cancer 1986; 38:339–344.
48. WHO Collaborative Study of Neoplasia and Steroid Contraceptives: Invasive cervical cancer and combined oral contraceptives. Br Med J 1985; 290:961–965.
49. Rooks JB, Ory HW, Ishak KG, Strauss LT, Greenspan JR, Hill AP, Tyler CW. Epidemiology of hepatocellular adenoma: the role of oral contraceptive use. JAMA 1979; 242:644–648.
50. Bein NN, Goldsmith HS. Recurrent massive hemorrhage from benign hepatic tumors secondary to oral contraceptives. Br J Surg 1977; 64:433–435.
51. Klatskin G. Hepatic tumors: possible relationship to use of oral contraceptives. Gastroenterology 1977; 73:386–394.
52. Henderson BE, Preston-Martin S, Edmondson HA, Peters RL, Pike MC. Hepatocellular carcinoma and oral contraceptives. Br J Cancer 1983; 48:437–440.
53. Neuberger J, Forman D, Doll R, Williams R. Oral contraceptives and hepatocellular carcinoma. Br Med J 1986; 292:1355–1357.
54. Forman D, Vincent TJ, Doll R. Cancer of the liver and oral contraceptives. Br Med J 1986; 292:1357–1361.
55. Harlap S, Eldor J. Births following oral contraceptive failures. Obstet Gynecol 1980; 55:447–452.
56. Savolainen E, Saksela E, Saxen L. Teratogenic hazards of oral contraceptives analyzed in a national malformation register. Am J Obstet Gynecol 1981; 140:521–524.
57. Janerich DT, Piper JM, Glebatis DM. Oral contraceptives and birth defects. Am J Epidemiol 1980; 112:73–79.
58. Ferencz C, Matanoski GM, Wilson PD, Rubin JD, Neill CA, Gutberlet R. Maternal hormone therapy and congenital heart disease. Teratology 1980; 21:225–239.
59. Rothman KJ, Fyler DC, Goldblatt A, Kreidberg MB. Exogenous hormones and other drug exposures of children with congenital heart disease. Am J Epidemiol 1979; 109:433–439.
60. Boston Collaborative Drug Surveillance Program: Oral contraceptives and venous thromboembolic disease, surgically confirmed gallbladder disease, and breast tumors. Lancet 1973; 1:1399–1404.
61. Royal College of General Practitioners: Oral contraceptives and health. New York, Pittman 1974.
62. Layde PM, Vessey MP, Yeates D. Risk of gallbladder disease: a cohort study of young women attending family planning clinics. J Epidemiol Community Health 1982; 36:274–278.
63. Rome Group for Epidemiology and Prevention of Cholelithiasis (GREPCO): Prevalence of gallstone disease in an Italian adult female population. Am J Epidemiol 1984; 119:796–805.
64. Storm BL, Tamragouri RT, Morse ML, Lazar EL, West SL, Stolley PD, Jones JK. Oral contraceptives and other risk factors for gallbladder disease. Clin Pharmacol Ther 1986; 39:335–341.
65. Wynn V, Adams PW, Godsland IF, Melrose J, Niththyananthan R, Oakley NW, Seedj A. Comparison of effects of different combined oral contraceptive formulations on carbohydrate and lipid metabolism. Lancet 1979; 1:1045–1049.
66. Wynn V. Effect of progesterone and progestins on carbohydrate metabolism. In: Progesterone and Progestin. Bardin CW, Milgrom E, Mauvis-Jarvis P. eds. New York, Raven Press, 1983; pp. 395–410.
67. Perlman JA, Roussell-Briefel RG, Ezzati TM, Lieberknecht G. Oral glucose tolerance and the potency of oral contraceptive progestogens. J Chronic Dis 1985; 38:857–864.
68. Royal College of General Practitioners' Oral Contraception Study: Effect on hypertension and benign breast disease of progestogen component in combined oral contraceptives. Lancet 1977; 1:624.
69. Fisch IR, Frank J. Oral contraceptives and blood pressure. JAMA 1977; 237:2499–2503.
70. Laragh AJ. Oral contraceptive induced hypertension-nine years later. Am J Obstet Gynecol 1976; 126:141–147.
71. Ramcharan S, Peritz E, Pellegrin FA, Williams WT. Incidence of hypertension in the Walnut Creek Contraceptive Drug Study cohort: In: Pharmacology of steroid contraceptive drugs. Garattini S, Berendes HW. Eds. New York, Raven Press, 1977; pp. 277–288, (Monographs of the Mario Negri Institute for Pharmacological Research Milan.)
72. Stockley I. Interactions with oral contraceptives. J Pharm 1976; 216:140–143.
73. The Cancer and Steroid Hormone Study of the Centers for Disease Control and the National Institute of Child Health and Human Development: Oral contraceptive use and the risk of ovarian cancer. JAMA 1983; 249:1596–1599.
74. The Cancer and Steroid Hormone Study of the Centers for Disease Control and the National Institute of Child Health and Human Development: Combination oral contraceptive use and the risk of endometrial cancer. JAMA 1987; 257:796–800.
75. Ory HW. Functional ovarian cysts and oral contraceptives: negative association confirmed surgically. JAMA 1974; 228:68–69.
76. Ory HW, Cole P, MacMahon B, Hoover R. Oral contraceptives and reduced risk of benign breast disease. N Engl J Med 1976; 294:419–422.
77. Ory HW. The noncontraceptive health benefits from oral contraceptive use. Fam Plann Perspect 1982; 14:182–184.
78. Ory HW, Forrest JD, Lincoln R. Making choices: Evaluating the health risks and benefits of birth control methods. New York, The Alan Guttmacher Institute, 1983; p. 1.
79. Schlesselman J, Stadel BV, Murray P, Lai S. Breast cancer in relation to early use of oral contraceptives. JAMA 1988; 259:1828–1833.
80. Hennekens CH, Speizer FE, Lipnick RJ, Rosner B, Bain C, Belanger C, Stampfer MJ, Willett W, Peto R. A case-control study of oral contraceptive use and breast cancer. JNCI 1984; 72:39–42.
81. LaVecchia C, Decarli A, Fasoli M, Franceschi S, Gentile A, Negri E, Parazzini F, Tognoni G. Oral contraceptives and cancers of the breast and of the female genital tract. Interim results from a case-control study. Br J Cancer 1986; 54:311–317.
82. Meirik O, Lund E, Adami H, Bergstrom R, Christoffersen T, Bergsjo P. Oral contraceptive use and breast cancer in young women. A Joint National Case-control study in Sweden and Norway. Lancet 1986; 11:650–654.
83. Kay CR, Hannaford PC. Breast cancer and the pill-A further report from the Royal College of General Practitioners' oral contraception study. Br J Cancer 1988; 58:675–680.
84. Stadel BV, Lai S, Schlesselman JJ, Murray P. Oral contraceptives and premenopausal breast cancer in nulliparous women. Contraception 1988; 38:287–299.
85. Miller DR, Rosenberg L, Kaufman DW, Stolley P, Warshauer ME, Shapiro S. Breast cancer before age 45 and oral contraceptive use: New Findings. Am J Epidemiol 1989; 129:269–280.
86. The UK National Case-Control Study Group, Oral contraceptive use and breast cancer risk in young women. Lancet 1989; 1:973–982.
87. Schlesselman JJ. Cancer of the breast and reproductive tract in relation to use of oral contraceptives. Contraception 1989; 40:1–38.
88. Vessey MP, McPherson K, Villard-Mackintosh L, Yeates D. Oral contraceptives and breast cancer: latest findings in a large cohort study. Br J Cancer 1989; 59:613–617.
89. Jick SS, Walker AM, Stergachis A, Jick H. Oral contraceptives and breast cancer. Br J Cancer 1989; 59:618–621.
90. Collaborative Group on Hormonal Factors in Breast Cancer. Breast cancer and hormonal contraceptives: collaborative reanalysis of individual data on 53,297 women with breast cancer and 100,239 women without breast cancer from 54 epidemiological studies. Lancet 1996; 347:1713–1727.
91. Palmer JR, Rosenberg L, Kaufman DW, Warshauer ME, Stolley P, Shapiro S. Oral Contraceptive Use and Liver Cancer. Am J Epidemiol 1989; 130:878–882.
92. Improving access to quality care in family planning: Medical eligibility criteria for contraceptive use. Geneva, WHO, Family and Reproductive Health, 1996.
93. Bork K, Fischer B, DeWald G. Recurrent episodes of skin angioedema and severe attacks of abdominal pain induced by oral contraceptives or hormone replacement therapy. Am J Med 2003;114:294–298.
94. Van Giersbergen PLM, Halabi A, Dingemanse J. Pharmacokinetic interaction between bosentan and the oral contraceptives norethisterone and ethinyl estradiol. Int J Clin Pharmacol Ther 2006;44(3):113–118.
95. Christensen J, Petrenaite V, Atterman J, et al. Oral contraceptives induce lamotrigine metabolism: evidence from a double-blind, placebo-controlled trial. Epilepsia 2007;48(3):484–489.

BRIEF SUMMARY PATIENT PACKAGE INSERT

Oral contraceptives, also known as "birth control pills" or "the pill," are taken to prevent pregnancy and when taken correctly without missing any pills, have a failure rate of approximately 1% per year. The typical failure rate is approximately 5% per year when women who miss pills are included. For most women oral contraceptives are also free of serious or unpleasant side effects. However, forgetting to take pills considerably increases the chances of pregnancy.

For the majority of women, oral contraceptives can be taken safely. But there are some women who are at high risk of developing certain serious diseases that can be fatal or may cause temporary or permanent disability. The risks associated with taking oral contraceptives increase significantly if you:

- smoke
- have high blood pressure, diabetes, high cholesterol
- have or have had clotting disorders, heart attack, stroke, angina pectoris, cancer of the breast or sex organs, jaundice or malignant or benign liver tumors.

Although cardiovascular disease risks may be increased with oral contraceptive use after age 40 in healthy, non-smoking women (even with the newer low-dose formulations), there are also greater potential health risks associated with pregnancy in older women.

You should not take the pill if you suspect you are pregnant or have unexplained vaginal bleeding.

BOXED WARNING

Cigarette smoking increases the risk of serious cardiovascular side effects from oral contraceptive use. This risk increases with age and with heavy smoking (15 or more cigarettes per day) and is quite marked in women over 35 years of age. Women who use oral contraceptives are strongly advised not to smoke.

Most side effects of the pill are not serious. The most common such effects are nausea, vomiting, bleeding between menstrual periods, weight gain, breast tenderness, and difficulty wearing contact lenses. These side effects, especially nausea and vomiting, may subside within the first three months of use.

The serious side effects of the pill occur very infrequently, especially if you are in good health and are young. However, you should know that the following medical conditions have been associated with or made worse by the pill:

1. Blood clots in the legs (thrombophlebitis), lungs (pulmonary embolism), stoppage or rupture of a blood vessel in the brain (stroke), blockage of blood vessels in the heart (heart attack or angina pectoris) or other organs of the body. As mentioned above, smoking increases the risk of heart attacks and strokes and subsequent serious medical consequences.
2. In rare cases, oral contraceptives can cause benign but dangerous liver tumors. These benign liver tumors can rupture and cause fatal internal bleeding. In addition, some studies report an increased risk of developing liver cancer. However, liver cancers are rare.
3. High blood pressure, although blood pressure usually returns to normal when the pill is stopped.

The symptoms associated with these serious side effects are discussed in the detailed leaflet given to you with your supply of pills. Notify your healthcare professional if you notice any unusual physical disturbances while taking the pill. In addition, drugs such as rifampin, as well as some anticonvulsants and some antibiotics may decrease oral contraceptive effectiveness.

Oral contraceptives may interact with lamotrigine (LAMICTAL®), an anticonvulsant used for epilepsy. This may increase the risk of seizures so your healthcare professional may need to adjust the dose of lamotrigine.

Various studies give conflicting reports on the relationship between breast cancer and oral contraceptive use. Oral contraceptive use may slightly increase your chance of having breast cancer diagnosed, particularly after using hormonal contraceptives at a younger age. After you stop using hormonal contraceptives, the chances of having breast cancer diagnosed begin to go back down. You should have regular breast examinations by a healthcare professional and examine your own breasts monthly.

Tell your healthcare professional if you have a family history of breast cancer or if you have had breast nodules or an abnormal mammogram. Women who currently have or have had breast cancer should not use oral contraceptives because breast cancer is usually a hormone-sensitive tumor.

Some studies have found an increase in the incidence of cancer of the cervix in women who use oral contraceptives. However, this finding may be related to factors other than the use of oral contraceptives. There is insufficient evidence to rule out the possibility that the pill may cause such cancers.

Taking the combination pill provides some important non-contraceptive benefits. These include less painful menstruation, less menstrual blood loss and anemia, fewer pelvic infections, and fewer cancers of the ovary and the lining of the uterus.

Be sure to discuss any medical condition you may have with your healthcare professional. Your healthcare professional will take a medical and family history before prescribing oral contraceptives and will examine you. The physical examination may be delayed to another time if you request it and the healthcare professional believes that it is a good medical practice to postpone it. You should be reexamined at least once a year while taking oral contraceptives. Your pharmacist should have given you the detailed patient information labeling which gives you further information which you should read and discuss with your healthcare professional.

This product (like all oral contraceptives) is intended to prevent pregnancy. It does not protect against transmission of HIV (AIDS) and other sexually transmitted diseases such as chlamydia, genital herpes, genital warts, gonorrhea, hepatitis B, and syphilis.

HOW TO TAKE THE PILL

IMPORTANT POINTS TO REMEMBER

BEFORE YOU START TAKING YOUR PILLS:

1. BE SURE TO READ THESE DIRECTIONS:
  Before you start taking your pills.
  Anytime you are not sure what to do.
2. THE RIGHT WAY TO TAKE THE PILL IS TO TAKE ONE PILL EVERY DAY AT THE SAME TIME.
  If you miss pills you could get pregnant. This includes starting the pack late.
  The more pills you miss, the more likely you are to get pregnant.
3. MANY WOMEN HAVE SPOTTING OR LIGHT BLEEDING, OR MAY FEEL SICK TO THEIR STOMACH DURING THE FIRST 1–3 PACKS OF PILLS. If you feel sick to your stomach, do not stop taking the pill. The problem will usually go away. If it doesn't go away, check with your healthcare professional.
4. MISSING PILLS CAN ALSO CAUSE SPOTTING OR LIGHT BLEEDING, even when you make up these missed pills.
  On the days you take 2 pills to make up for missed pills, you could also feel a little sick to your stomach.
5. IF YOU HAVE VOMITING OR DIARRHEA, or IF YOU TAKE SOME MEDICINES, including some antibiotics, your pills may not work as well. Use a back-up method (such as a condom or spermicide) until you check with your healthcare professional.
6. IF YOU HAVE TROUBLE REMEMBERING TO TAKE THE PILL, talk to your healthcare professional about how to make pill taking easier or about using another method of birth control.
7. IF YOU HAVE ANY QUESTIONS OR ARE UNSURE ABOUT THE INFORMATION IN THIS LEAFLET, call your healthcare professional.

BEFORE YOU START TAKING YOUR PILLS

1. DECIDE WHAT TIME OF DAY YOU WANT TO TAKE YOUR PILL.
  It is important to take it at about the same time every day.
2. LOOK AT YOUR PILL PACK.
  The pill pack has 7 white "active" pills, 7 light peach "active" pills and 7 peach "active" pills (with hormones) to take for 3 weeks. This is followed by 1 week of green "reminder" pills (without hormones).
3. ALSO FIND:
  1) where on the pack to start taking pills,
  2) in what order to take the pills.
4. BE SURE YOU HAVE READY AT ALL TIMES:
  ANOTHER KIND OF BIRTH CONTROL (such as a condom or spermicide) to use as a back-up method in case you miss pills.
  AN EXTRA, FULL PILL PACK.

WHEN TO START THE FIRST PACK OF PILLS

You have a choice of which day to start taking your first pack of pills. NECON 7/7/7® is available in a blister card with a tablet dispenser which is preset for a Sunday Start. Day 1 Start is also provided. Decide with your healthcare professional which is the best day for you. Pick a time of day that will be easy to remember.

SUNDAY START:

Take the first white "active" pill of the first pack on the Sunday after your period starts, even if you are still bleeding. If your period begins on Sunday, start the pack the same day.

Use another method of birth control such as a condom or spermicide as a back-up method if you have sex anytime from the Sunday you start your first pack until the next Sunday (7 days).

DAY 1 START:

Take the first white "active" pill of the first pack during the first 24 hours of your period.

You will not need to use a back-up method of birth control, since you are starting the pill at the beginning of your period.

WHAT TO DO DURING THE MONTH

1. TAKE ONE PILL AT THE SAME TIME EVERY DAY UNTIL THE PACK IS EMPTY.
  Do not skip pills even if you are spotting or bleeding between monthly periods or feel sick to your stomach (nausea). Do not skip pills even if you do not have sex very often.
2. WHEN YOU FINISH A PACK OR SWITCH YOUR BRAND OF PILLS:
  Start the next pack on the day after your last green "reminder" pill. Do not wait any days between packs.

WHAT TO DO IF YOU MISS PILLS

If you MISS 1 white, light peach, or peach "active" pill:

1. Take it as soon as you remember. Take the next pill at your regular time. This means you may take 2 pills in 1 day.
2. You do not need to use a back-up birth control method if you have sex.

If you MISS 2 white or light peach "active" pills in a row in WEEK 1 OR WEEK 2 of your pack:

1. Take 2 pills on the day you remember and 2 pills the next day.
2. Then take 1 pill a day until you finish the pack.
3. You COULD BECOME PREGNANT if you have sex in the 7 days after you miss pills. You MUST use another birth control method (such as a condom or spermicide) as a back-up method for those 7 days.

If you MISS 2 peach "active" pills in a row in THE 3RD WEEK:

1a. If you are a Sunday Starter:

Keep taking 1 pill every day until Sunday. On Sunday, THROW OUT the rest of the pack and start a new pack of pills that same day.

1b. If you are a Day 1 Starter:

THROW OUT the rest of the pill pack and start a new pack that same day.

2. You may not have your period this month but this is expected. However, if you miss your period 2 months in a row, call your healthcare professional because you might be pregnant.
3. You COULD BECOME PREGNANT if you have sex in the 7 days after you miss pills. You MUST use another birth control method (such as a condom or spermicide) as a back-up method for those 7 days.

If you MISS 3 OR MORE white, light peach, or peach "active" pills in a row (during the first 3 weeks):

1a. If you are a Sunday Starter:

Keep taking 1 pill every day until Sunday. On Sunday, THROW OUT the rest of the pack and start a new pack of pills that same day.

1b. If you are a Day 1 Starter:

THROW OUT the rest of the pill pack and start a new pack that same day.

2. You may not have your period this month but this is expected. However, if you miss your period 2 months in a row, call your healthcare professional because you might be pregnant.
3. You COULD BECOME PREGNANT if you have sex in the 7 days after you miss pills. You MUST use another birth control method (such as a condom or spermicide) as a back-up method for those 7 days.

A REMINDER
If you forget any of the 7 green "reminder" pills in Week 4:
THROW AWAY the pills you missed. Keep taking 1 pill each day until the pack is empty. You do not need a back-up method.

FINALLY, IF YOU ARE STILL NOT SURE WHAT TO DO ABOUT THE PILLS YOU HAVE MISSED:
Use a BACK-UP METHOD anytime you have sex.
KEEP TAKING ONE "ACTIVE" PILL EACH DAY until you can reach your healthcare professional.

INSTRUCTIONS FOR USE

1. Open the compact. Place the blister card into the compact, with the tablets facing up, so that the V notch in the blister card matches up with the V-shaped post at the top of the compact. Press down firmly on each edge of the blister card and make sure that the edge of the card is firmly seated under each of the nibs inside the compact (see picture).

There are 7 white "active" pills, 7 light peach "active" pills, 7 peach "active" pills and 7 green "reminder" pills.

2. If you are to start pill taking on Sunday, take your first white "active" pill on the first Sunday after your menstrual period begins. If your period begins on Sunday, take your first white "active" pill that day. Remove the first white "active" pill at the top of the dispenser (Sunday) by pressing the pill through the hole in the bottom of the dispenser.
3. If you are to start pill taking on a day other than Sunday, the enclosed calendar label has been provided and will be placed over the calendar in the center of the blister card. To put the label in place, identify your correct starting day, locate that day printed in blue on the label, and line your blue starting day up with the first white "active" pill which is directly under the V notch at the top of the dispenser. Remove the label from the backing. Press the center of the label down onto the center of the printed calendar. Remove that white "active" pill by pressing the pill through the hole in the bottom of the dispenser.
4. Continue taking one "active" pill daily, clockwise, until no "active" pills remain in the outer ring.
5. The next day take the green "reminder" pill from the inner ring that corresponds with the day of the week it happens to be. Take a green "reminder" pill each day until all seven pills are taken. During this time your period should begin.
6. After you have taken all the green "reminder" pills, insert a new blister card (see "How to Insert New Blister Card" below) into the tablet dispenser and take the first white "active" pill on the next day, even if your period is not yet over.

HOW TO INSERT NEW BLISTER CARD

1. Lift the empty blister card out of the tablet dispenser.
  Insert the new blister card so that the V notch in the blister card is at the top of the dispenser. Press the blister card down so that it fits firmly under the nibs.

DETAILED PATIENT LABELING

PLEASE NOTE: This labeling is revised from time to time as important new medical information becomes available. Therefore, please review this labeling carefully.

The following oral contraceptive product contains a combination of an estrogen and progestogen, the two kinds of female hormones:

NECON 7/7/7®

Each white tablet contains 0.5 mg norethindrone and 0.035 mg ethinyl estradiol. Each light peach tablet contains 0.75 mg norethindrone and 0.035 mg ethinyl estradiol. Each peach tablet contains 1 mg norethindrone and 0.035 mg ethinyl estradiol. Each green tablet contains inert ingredients.

INTRODUCTION

Any woman who considers using oral contraceptives (the birth control pill or the pill) should understand the benefits and risks of using this form of birth control. This patient labeling will give you much of the information you will need to make this decision and will also help you determine if you are at risk of developing any of the serious side effects of the pill. It will tell you how to use the pill properly so that it will be as effective as possible. However, this labeling is not a replacement for a careful discussion between you and your healthcare professional. You should discuss the information provided in this labeling with him or her, both when you first start taking the pill and during your revisits. You should also follow your healthcare professional's advice with regard to regular check-ups while you are on the pill.

EFFECTIVENESS OF ORAL CONTRACEPTIVES

Oral contraceptives or "birth control pills" or "the pill" are used to prevent pregnancy and are more effective than other non-surgical methods of birth control. When they are taken correctly without missing any pills, the chance of becoming pregnant is approximately 1% (1 pregnancy per 100 women per year of use). Typical failure rates are approximately 5% per year including women who do not always take the pills exactly as directed. The chance of becoming pregnant increases with each missed pill during a menstrual cycle.

In comparison, typical failure rates for other methods of birth control during the first year of use are as follows:

Implant: <1%
Injection: <1%
IUD: 1 to 2%
Diaphragm with spermicides: 20%
Spermicides alone: 26%
Vaginal sponge: 20 to 40%
Female sterilization: <1%

Male sterilization: <1%
Cervical Cap with spermicides: 20 to 40%
Condom alone (male): 14%
Condom alone (female): 21%
Periodic abstinence: 25%
Withdrawal: 19%
No methods: 85%

WHO SHOULD NOT TAKE ORAL CONTRACEPTIVES

BOXED WARNING

Cigarette smoking increases the risk of serious cardiovascular side effects from oral contraceptive use. This risk increases with age and with heavy smoking (15 or more cigarettes per day) and is quite marked in women over 35 years of age. Women who use oral contraceptives are strongly advised not to smoke.

Some women should not use the pill. For example, you should not take the pill if you have any of the following conditions:

- A history of heart attack or stroke
- Blood clots in the legs (thrombophlebitis), lungs (pulmonary embolism), or eyes
- A history of blood clots in the deep veins of your legs
- Chest pain (angina pectoris)
- Known or suspected breast cancer or cancer of the lining of the uterus, cervix or vagina
- Unexplained vaginal bleeding (until a diagnosis is reached by your healthcare professional)
- Yellowing of the whites of the eyes or of the skin (jaundice) during pregnancy or during previous use of the pill
- Liver tumor (benign or cancerous)
- Known or suspected pregnancy
- Valvular heart disease with complications
- Severe hypertension
- Diabetes with vascular involvement
- Headaches with focal neurological symptoms
- If you plan to have surgery with prolonged bed rest
- Hypersensitivity to any component of this product.

Tell your healthcare professional if you have ever had any of these conditions. Your healthcare professional can recommend a safer method of birth control.

OTHER CONSIDERATIONS BEFORE TAKING ORAL CONTRACEPTIVES

Tell your healthcare professional if you have or have had:

- Breast nodules, fibrocystic disease of the breast, an abnormal breast x-ray or mammogram
- Diabetes
- Elevated cholesterol or triglycerides
- High blood pressure
- Migraine or other headaches or epilepsy
- Mental depression
- Gallbladder, liver, heart or kidney disease
- History of scanty or irregular menstrual periods

Women with any of these conditions should be checked often by their healthcare professional if they choose to use oral contraceptives.

Also, be sure to inform your healthcare professional if you smoke or are on any medications.

RISKS OF TAKING ORAL CONTRACEPTIVES

1. Risk of developing blood clots

Blood clots and blockage of blood vessels are one of the most serious side effects of taking oral contraceptives and can cause death or serious disability. In particular, a clot in the legs can cause thrombophlebitis and a clot that travels to the lungs can cause a sudden blocking of the vessel carrying blood to the lungs. Rarely, clots occur in the blood vessels of the eye and may cause blindness, double vision, or impaired vision.

If you take oral contraceptives and need elective surgery, need to stay in bed for a prolonged illness or injury or have recently delivered a baby, you may be at risk of developing blood clots. You should consult your healthcare professional about stopping oral contraceptives three to four weeks before surgery and not taking oral contraceptives for two weeks after surgery or during bed rest. You should also not take oral contraceptives soon after delivery of a baby. It is advisable to wait for at least four weeks after delivery if you are not breastfeeding or four weeks after a second trimester abortion. If you are breastfeeding, you should wait until you have weaned your child before using the pill. (See also the section on Breastfeeding in General Precautions.)

The risk of circulatory disease in oral contraceptive users may be higher in users of high-dose pills and may be greater with longer duration of oral contraceptive use. In addition, some of these increased risks may continue for a number of years after stopping oral contraceptives. The risk of abnormal blood clotting increases with age in both users and nonusers of oral contraceptives, but the increased risk from the oral contraceptive appears to be present at all ages. For women aged 20 to 44, it is estimated that about 1 in 2,000 using oral contraceptives will be hospitalized each year because of abnormal clotting. Among nonusers in the same age group, about 1 in 20,000 would be hospitalized each year. For oral contraceptive users in general, it has been estimated that in women between the ages of 15 and 34 the risk of death due to a circulatory disorder is about 1 in 12,000 per year, whereas for nonusers the rate is about 1 in 50,000 per year. In the age group 35 to 44, the risk is estimated to be about 1 in 2,500 per year for oral contraceptive users and about 1 in 10,000 per year for nonusers.

2. Heart attacks and strokes

Oral contraceptives may increase the tendency to develop strokes (stoppage or rupture of blood vessels in the brain) and angina pectoris and heart attacks (blockage of blood vessels in the heart). Any of these conditions can cause death or serious disability.

Smoking greatly increases the possibility of suffering heart attacks and strokes. Furthermore, smoking and the use of oral contraceptives greatly increase the chances of developing and dying of heart disease.

3. Gallbladder disease

Oral contraceptive users probably have a greater risk than nonusers of having gallbladder disease, although this risk may be related to pills containing high doses of estrogens.

4. Liver tumors

In rare cases, oral contraceptives can cause benign but dangerous liver tumors. These benign liver tumors can rupture and cause fatal internal bleeding. In addition, some studies report an increased risk of developing liver cancer. However, liver cancers are rare.

5. Cancer of the reproductive organs and breasts

Various studies give conflicting reports on the relationship between breast cancer and oral contraceptive use. Oral contraceptive use may slightly increase your chance of having breast cancer diagnosed, particularly after using hormonal contraceptives at a younger age. After you stop using hormonal contraceptives, the chances of having breast cancer diagnosed begin to go back down. You should have regular breast examinations by a healthcare professional and examine your own breasts monthly. Tell your healthcare professional if you have a family history of breast cancer or if you have had breast nodules or an abnormal mammogram. Women who currently have or have had breast cancer should not use oral contraceptives because breast cancer is usually a hormone-sensitive tumor.

Some studies have found an increase in the incidence of cancer of the cervix in women who use oral contraceptives. However, this finding may be related to factors other than the use of oral contraceptives. There is insufficient evidence to rule out the possibility that the pill may cause such cancers.

ESTIMATED RISK OF DEATH FROM A BIRTH CONTROL METHOD OR PREGNANCY

All methods of birth control and pregnancy are associated with a risk of developing certain diseases which may lead to disability or death. An estimate of the number of deaths associated with different methods of birth control and pregnancy has been calculated and is shown in the following table.

ANNUAL NUMBER OF BIRTH-RELATED OR METHOD-RELATED DEATHS ASSOCIATED WITH CONTROL OF FERTILITY PER 100,000 NONSTERILE WOMEN, BY FERTILITY CONTROL METHOD ACCORDING TO AGE
Method of control and outcome | 15–19 | 20–24 | 25–29 | 30–34 | 35–39 | 40–44
No fertility-control methods [Deaths are birth-related] | 7.0 | 7.4 | 9.1 | 14.8 | 25.7 | 28.2
Oral contraceptives non-smoker [Deaths are method-related] | 0.3 | 0.5 | 0.9 | 1.9 | 13.8 | 31.6
Oral contraceptives smoker | 2.2 | 3.4 | 6.6 | 13.5 | 51.1 | 117.2
IUD | 0.8 | 0.8 | 1.0 | 1.0 | 1.4 | 1.4
Condom | 1.1 | 1.6 | 0.7 | 0.2 | 0.3 | 0.4
Diaphragm/spermicide | 1.9 | 1.2 | 1.2 | 1.3 | 2.2 | 2.8
Periodic abstinence | 2.5 | 1.6 | 1.6 | 1.7 | 2.9 | 3.6

In the above table, the risk of death from any birth control method is less than the risk of childbirth, except for oral contraceptive users over the age of 35 who smoke and pill users over the age of 40 even if they do not smoke. It can be seen in the table that for women aged 15 to 39, the risk of death was highest with pregnancy (7–26 deaths per 100,000 women, depending on age). Among pill users who do not smoke, the risk of death was always lower than that associated with pregnancy for any age group, although over the age of 40, the risk increases to 32 deaths per 100,000 women, compared to 28 associated with pregnancy at that age. However, for pill users who smoke and are over the age of 35, the estimated number of deaths exceeds those for other methods of birth control. If a woman is over the age of 40 and smokes, her estimated risk of death is four times higher (117/100,000 women) than the estimated risk associated with pregnancy (28/100,000 women) in that age group.

The suggestion that women over 40 who do not smoke should not take oral contraceptives is based on information from older, higher-dose pills. An Advisory Committee of the FDA discussed this issue in 1989 and recommended that the benefits of low-dose oral contraceptive use by healthy, non-smoking women over 40 years of age may outweigh the possible risks.

WARNING SIGNALS

If any of these adverse effects occur while you are taking oral contraceptives, call your healthcare professional immediately:

- Sharp chest pain, coughing of blood, or sudden shortness of breath (indicating a possible clot in the lung)
- Pain in the calf (indicating a possible clot in the leg)
- Crushing chest pain or heaviness in the chest (indicating a possible heart attack)
- Sudden severe headache or vomiting, dizziness or fainting, disturbances of vision or speech, weakness, or numbness in an arm or leg (indicating a possible stroke)
- Sudden partial or complete loss of vision (indicating a possible clot in the eye)
- Breast lumps (indicating possible breast cancer or fibrocystic disease of the breast; ask your healthcare professional to show you how to examine your breasts)
- Severe pain or tenderness in the stomach area (indicating a possibly ruptured liver tumor)
- Difficulty in sleeping, weakness, lack of energy, fatigue, or change in mood (possibly indicating severe depression)
- Jaundice or a yellowing of the skin or eyeballs, accompanied frequently by fever, fatigue, loss of appetite, dark colored urine, or light colored bowel movements (indicating possible liver problems)

SIDE EFFECTS OF ORAL CONTRACEPTIVES

1. Vaginal bleeding

Irregular vaginal bleeding or spotting may occur while you are taking the pills. Irregular bleeding may vary from slight staining between menstrual periods to breakthrough bleeding which is a flow much like a regular period. Irregular bleeding occurs most often during the first few months of oral contraceptive use, but may also occur after you have been taking the pill for some time. Such bleeding may be temporary and usually does not indicate any serious problems. It is important to continue taking your pills on schedule. If the bleeding occurs in more than one cycle or lasts for more than a few days, talk to your healthcare professional.

2. Contact lenses

If you wear contact lenses and notice a change in vision or an inability to wear your lenses, contact your healthcare professional.

3. Fluid retention

Oral contraceptives may cause edema (fluid retention) with swelling of the fingers or ankles and may raise your blood pressure. If you experience fluid retention, contact your healthcare professional.

4. Melasma

A spotty darkening of the skin is possible, particularly of the face, which may persist.

5. Other side effects

Other side effects may include nausea and vomiting, change in appetite, headache, nervousness, depression, dizziness, loss of scalp hair, rash, vaginal infections and allergic reactions.

If any of these side effects bother you, call your healthcare professional.

GENERAL PRECAUTIONS

1. Missed periods and use of oral contraceptives before or during early pregnancy

There may be times when you may not menstruate regularly after you have completed taking a cycle of pills. If you have taken your pills regularly and miss one menstrual period, continue taking your pills for the next cycle but be sure to inform your healthcare professional before doing so. If you have not taken the pills daily as instructed and missed a menstrual period, you may be pregnant. If you missed two consecutive menstrual periods, you may be pregnant. Check with your healthcare professional immediately to determine whether you are pregnant. Do not continue to take oral contraceptives until you are sure you are not pregnant, but continue to use another method of contraception.

There is no conclusive evidence that oral contraceptive use is associated with an increase in birth defects, when taken inadvertently during early pregnancy. Previously, a few studies had reported that oral contraceptives might be associated with birth defects, but these findings have not been seen in more recent studies. Nevertheless, oral contraceptives should not be used during pregnancy. You should check with your healthcare professional about risks to your unborn child of any medication taken during pregnancy.

2. While breastfeeding

If you are breastfeeding, consult your healthcare professional before starting oral contraceptives. Some of the drug will be passed on to the child in the milk. A few adverse effects on the child have been reported, including yellowing of the skin (jaundice) and breast enlargement. In addition, combined oral contraceptives may decrease the amount and quality of your milk. If possible, do not use combined oral contraceptives while breastfeeding. You should use another method of contraception since breastfeeding provides only partial protection from becoming pregnant and this partial protection decreases significantly as you breastfeed for longer periods of time. You should consider starting combined oral contraceptives only after you have weaned your child completely.

3. Laboratory tests

If you are scheduled for any laboratory tests, tell your healthcare professional you are taking birth control pills. Certain blood tests may be affected by birth control pills.

4. Drug interactions

Certain drugs may interact with birth control pills to make them less effective in preventing pregnancy or cause an increase in breakthrough bleeding. Such drugs include rifampin, drugs used for epilepsy such as barbiturates (for example, phenobarbital), topiramate (TOPAMAX®), carbamazepine (Tegretol® is one brand of this drug), phenytoin (Dilantin® is one brand of this drug), phenylbutazone (Butazolidin® is one brand), certain drugs used in the treatment of HIV or AIDS, and possibly certain antibiotics. Medicine for pulmonary hypertension, such as bosentan (Tracleer®). Pregnancies and breakthrough bleeding have been reported by users of combined hormonal contraceptives who also used some form of the herbal supplement St. John's Wort. Hormonal contraceptives may interact with lamotrigine (LAMICTAL®), an anticonvulsant used for epilepsy. This may increase the risk of seizures so your healthcare professional may need to adjust the dose of lamotrigine. You may need to use additional contraception when you take other products which can make oral contraceptives less effective. Be sure to tell your healthcare professional if you are taking or start taking any medications while taking birth control pills.

5. Sexually transmitted diseases

This product (like all oral contraceptives) is intended to prevent pregnancy. It does not protect against transmission of HIV (AIDS) and other sexually transmitted diseases such as chlamydia, genital herpes, genital warts, gonorrhea, hepatitis B, and syphilis.

HOW TO TAKE THE PILL

IMPORTANT POINTS TO REMEMBER

BEFORE YOU START TAKING YOUR PILLS:

1. BE SURE TO READ THESE DIRECTIONS:
  Before you start taking your pills.
  Anytime you are not sure what to do.
2. THE RIGHT WAY TO TAKE THE PILL IS TO TAKE ONE PILL EVERY DAY AT THE SAME TIME.
  If you miss pills you could get pregnant. This includes starting the pack late.
  The more pills you miss, the more likely you are to get pregnant.
3. MANY WOMEN HAVE SPOTTING OR LIGHT BLEEDING, OR MAY FEEL SICK TO THEIR STOMACH DURING THE FIRST 1–3 PACKS OF PILLS. If you feel sick to your stomach, do not stop taking the pill. The problem will usually go away. If it doesn't go away, check with your healthcare professional.
4. MISSING PILLS CAN ALSO CAUSE SPOTTING OR LIGHT BLEEDING, even when you make up these missed pills.
  On the days you take 2 pills to make up for missed pills, you could also feel a little sick to your stomach.
5. IF YOU HAVE VOMITING OR DIARRHEA or IF YOU TAKE SOME MEDICINES, including some antibiotics, your pills may not work as well. Use a back-up method (such as a condom or spermicide) until you check with your healthcare professional.
6. IF YOU HAVE TROUBLE REMEMBERING TO TAKE THE PILL, talk to your healthcare professional about how to make pill taking easier or about using another method of birth control.
7. IF YOU HAVE ANY QUESTIONS OR ARE UNSURE ABOUT THE INFORMATION IN THIS LEAFLET, call your healthcare professional.

BEFORE YOU START TAKING YOUR PILLS

1. DECIDE WHAT TIME OF DAY YOU WANT TO TAKE YOUR PILL.
  It is important to take it at about the same time every day.
2. LOOK AT YOUR PILL PACK:
  The pill pack has 7 white "active" pills, 7 light peach "active" pills and 7 peach "active" pills (with hormones) to take for 3 weeks. This is followed by 1 week of green "reminder" pills (without hormones).
3. ALSO FIND:
  1) where on the pack to start taking pills,
  2) in what order to take the pills.
  CHECK PICTURE OF PILL PACK AND ADDITIONAL INSTRUCTIONS FOR USING THIS PACKAGE IN THE BRIEF SUMMARY PATIENT PACKAGE INSERT.
4. BE SURE YOU HAVE READY AT ALL TIMES:
  ANOTHER KIND OF BIRTH CONTROL (such as a condom or spermicide) to use as a back-up method in case you miss pills.
  AN EXTRA, FULL PILL PACK.

WHEN TO START THE FIRST PACK OF PILLS

You have a choice of which day to start taking your first pack of pills. NECON 7/7/7® is available in a blister card with a tablet dispenser which is preset for a Sunday Start. Day 1 Start is also provided. Decide with your healthcare professional which is the best day for you. Pick a time of day that will be easy to remember.

SUNDAY START:

Take the first white "active" pill of the first pack on the Sunday after your period starts, even if you are still bleeding. If your period begins on Sunday, start the pack the same day.

Use another method of birth control such as a condom or spermicide as a back-up method if you have sex anytime from the Sunday you start your first pack until the next Sunday (7 days).

DAY 1 START:

Take the first white "active" pill of the first pack during the first 24 hours of your period.

You will not need to use a back-up method of birth control, since you are starting the pill at the beginning of your period.

WHAT TO DO DURING THE MONTH

1. TAKE ONE PILL AT THE SAME TIME EVERY DAY UNTIL THE PACK IS EMPTY.
  Do not skip pills even if you are spotting or bleeding between monthly periods or feel sick to your stomach (nausea).
  Do not skip pills even if you do not have sex very often.
2. WHEN YOU FINISH A PACK OR SWITCH YOUR BRAND OF PILLS:
  Start the next pack on the day after your last green "reminder" pill. Do not wait any days between packs.

WHAT TO DO IF YOU MISS PILLS

If you MISS 1 white, light peach, or peach "active" pill:

1. Take it as soon as you remember. Take the next pill at your regular time. This means you may take 2 pills in 1 day.
2. You do not need to use a back-up birth control method if you have sex.

If you MISS 2 white or light peach "active" pills in a row in WEEK 1 OR WEEK 2 of your pack:

1. Take 2 pills on the day you remember and 2 pills the next day.
2. Then take 1 pill a day until you finish the pack.
3. You COULD BECOME PREGNANT if you have sex in the 7 days after you miss pills. You MUST use another birth control method (such as a condom or spermicide) as a back-up method for those 7 days.

If you MISS 2 peach "active" pills in a row in THE 3RD WEEK:

1a. If you are a Sunday Starter:

Keep taking 1 pill every day until Sunday. On Sunday, THROW OUT the rest of the pack and start a new pack of pills that same day.

1b. If you are a Day 1 Starter:

THROW OUT the rest of the pill pack and start a new pack that same day.

2. You may not have your period this month but this is expected. However, if you miss your period 2 months in a row, call your healthcare professional because you might be pregnant.
3. You COULD BECOME PREGNANT if you have sex in the 7 days after you miss pills. You MUST use another birth control method (such as a condom or spermicide) as a back-up method for those 7 days.

If you MISS 3 OR MORE white, light peach, or peach "active" pills in a row (during the first 3 weeks):

1a. If you are a Sunday Starter:

Keep taking 1 pill every day until Sunday. On Sunday, THROW OUT the rest of the pack and start a new pack of pills that same day.

1b. If you are a Day 1 Starter:

THROW OUT the rest of the pill pack and start a new pack that same day.

2. You may not have your period this month but this is expected. However, if you miss your period 2 months in a row, call your healthcare professional because you might be pregnant.
3. You COULD BECOME PREGNANT if you have sex in the 7 days after you miss pills. You MUST use another birth control method (such as a condom or spermicide) as a back-up method for those 7 days.

A REMINDER
If you forget any of the 7 green "reminder" pills in Week 4:
THROW AWAY the pills you missed. Keep taking 1 pill each day until the pack is empty. You do not need a back-up method.

FINALLY, IF YOU ARE STILL NOT SURE WHAT TO DO ABOUT THE PILLS YOU HAVE MISSED:
Use a BACK-UP METHOD anytime you have sex.
KEEP TAKING ONE "ACTIVE" PILL EACH DAY until you can reach your healthcare professional.

PREGNANCY DUE TO PILL FAILURE

Combined Oral Contraceptives

The incidence of pill failure resulting in pregnancy is approximately one percent (i.e., one pregnancy per 100 women per year) if taken every day as directed, but more typical failure rates are 5%. If failure does occur, the risk to the fetus is minimal.

PREGNANCY AFTER STOPPING THE PILL

There may be some delay in becoming pregnant after you stop using oral contraceptives, especially if you had irregular menstrual cycles before you used oral contraceptives. It may be advisable to postpone conception until you begin menstruating regularly once you have stopped taking the pill and desire pregnancy.

There does not appear to be any increase in birth defects in newborn babies when pregnancy occurs soon after stopping the pill.

OVERDOSAGE

Serious ill effects have not been reported following ingestion of large doses of oral contraceptives by young children. Overdosage may cause nausea and withdrawal bleeding in females. In case of overdosage, contact your healthcare professional or pharmacist.

OTHER INFORMATION

Your healthcare professional will take a medical and family history before prescribing oral contraceptives and will examine you. The physical examination may be delayed to another time if you request it and the healthcare professional believes that it is a good medical practice to postpone it. You should be reexamined at least once a year. Be sure to inform your healthcare professional if there is a family history of any of the conditions listed previously in this leaflet. Be sure to keep all appointments with your healthcare professional, because this is a time to determine if there are early signs of side effects of oral contraceptive use.

Do not use the drug for any condition other than the one for which it was prescribed. This drug has been prescribed specifically for you; do not give it to others who may want birth control pills.

HEALTH BENEFITS FROM ORAL CONTRACEPTIVES

In addition to preventing pregnancy, use of combined oral contraceptives may provide certain benefits. They are:

- menstrual cycles may become more regular
- blood flow during menstruation may be lighter and less iron may be lost.
  Therefore, anemia due to iron deficiency is less likely to occur.
- pain or other symptoms during menstruation may be encountered less frequently
- ectopic (tubal) pregnancy may occur less frequently
- noncancerous cysts or lumps in the breast may occur less frequently
- acute pelvic inflammatory disease may occur less frequently
- oral contraceptive use may provide some protection against developing two forms of cancer: cancer of the ovaries and cancer of the lining of the uterus.

If you want more information about birth control pills, ask your healthcare professional or pharmacist. They have a more technical leaflet called the Professional Labeling, which you may wish to read. The professional labeling is also published in a book entitled Physicians' Desk Reference, available in many book stores and public libraries.

Store at 25°C (77°F); excursions permitted to 15°–30°C (59°–86°F).

(LOGO)

Mfd.for:
Watson Laboratories, Inc.
A Subsidiary of Watson Pharmaceuticals, Inc.
Corona, CA 92880 USA

Mfd.by:
JOLLC
Manati, Puerto Rico
00674

Revised November 2010
635237005

PRINCIPAL DISPLAY PANEL -Necon 7/7/7 Carton

NDC 68258-5005-02

Necon 7/7/7®
(norethindrone and ethinyl estradiol tablets)
28

Each white tablet (7) contains 0.5 mg norethindrone and
0.035 mg ethinyl estradiol. Each light peach tablet (7) contains
0.75 mg norethindrone and 0.035 mg ethinyl estradiol. Each peach
tablet (7) contains 1 mg norethindrone and 0.035 mg ethinyl estradiol.
Each green tablet (7) contains inert ingredients.

6 Tablet Dispensers, 28 Tablets Each

Rx only